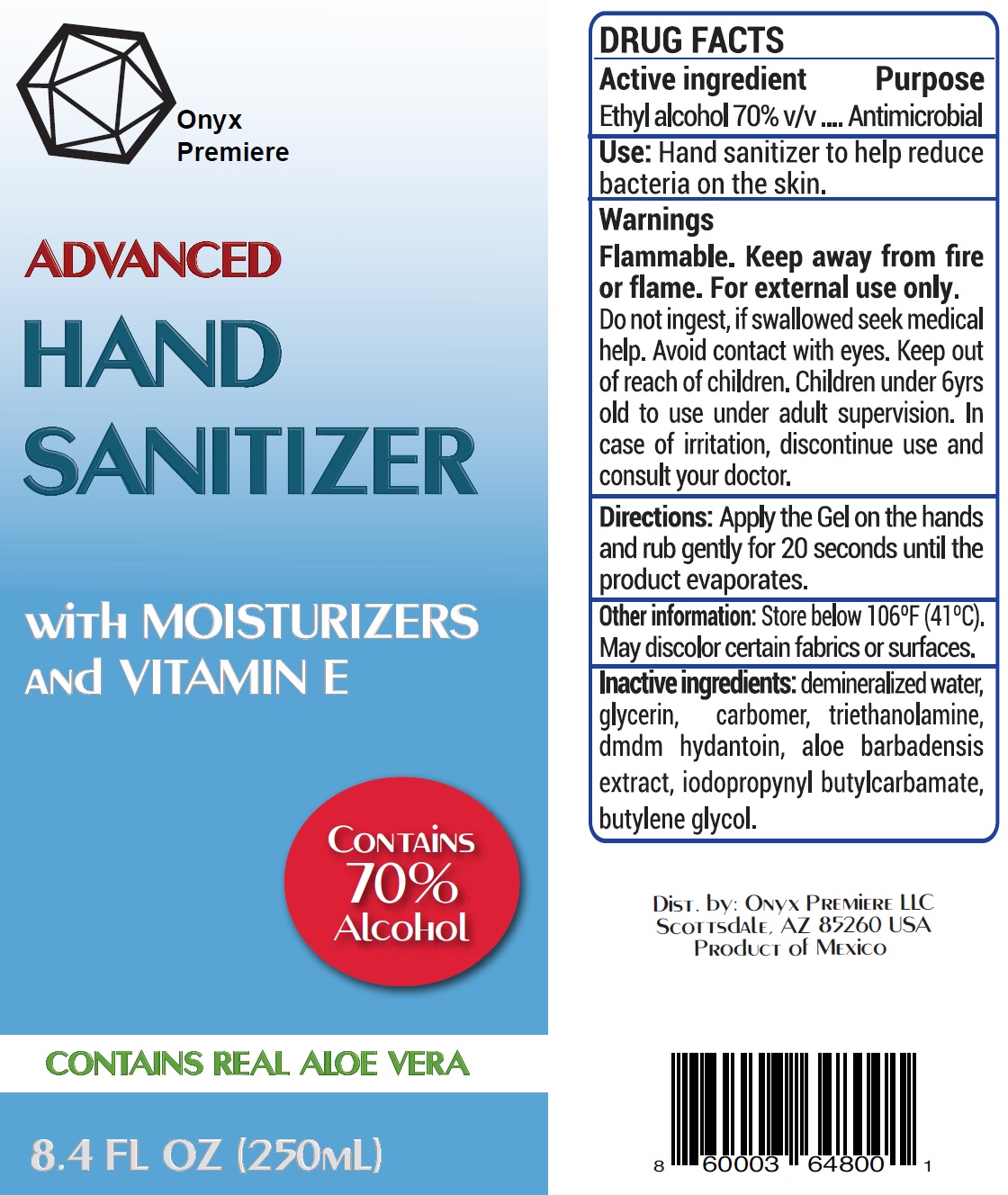 DRUG LABEL: Onyx Advanced Hand Sanitizer
NDC: 75403-000 | Form: GEL
Manufacturer: ONYX PREMIERE LLC
Category: otc | Type: HUMAN OTC DRUG LABEL
Date: 20200421

ACTIVE INGREDIENTS: ALCOHOL 0.7 mL/1 mL
INACTIVE INGREDIENTS: WATER; GLYCERIN; CARBOMER HOMOPOLYMER, UNSPECIFIED TYPE; TROLAMINE; DMDM HYDANTOIN; IODOPROPYNYL BUTYLCARBAMATE; BUTYLENE GLYCOL

Onyx Advanced Hand Sanitizer

Active ingredient

Ethyl alcohol 70% v/v

Purpose

Antimicrobial

Use:

Hand sanitizer to help reduce bacteria on the skin.

Warnings

Flammable. Keep away from fire or flame. For external use only.

Do not

ingest, if swallowed seek medical help. Avoid contact with eyes.

Keep out of reach of children.

Children under 6yrs old to use under adult supervision. In case of irritation, discontinue use and consult your doctor.

Directions:

Apply the Gel on the hands and rub gently for 20 seconds until the product evaporates.

Other information:

Store below 106°F (41°C).

May discolor certain fabrics or surfaces.

Inactive ingredients:

demineralized water, glycerin, carbomer, triethanolamine, dmdm hydantoin, aloe barbadensis extract, iodopropynyl butylcarbamate, butylene glycol.